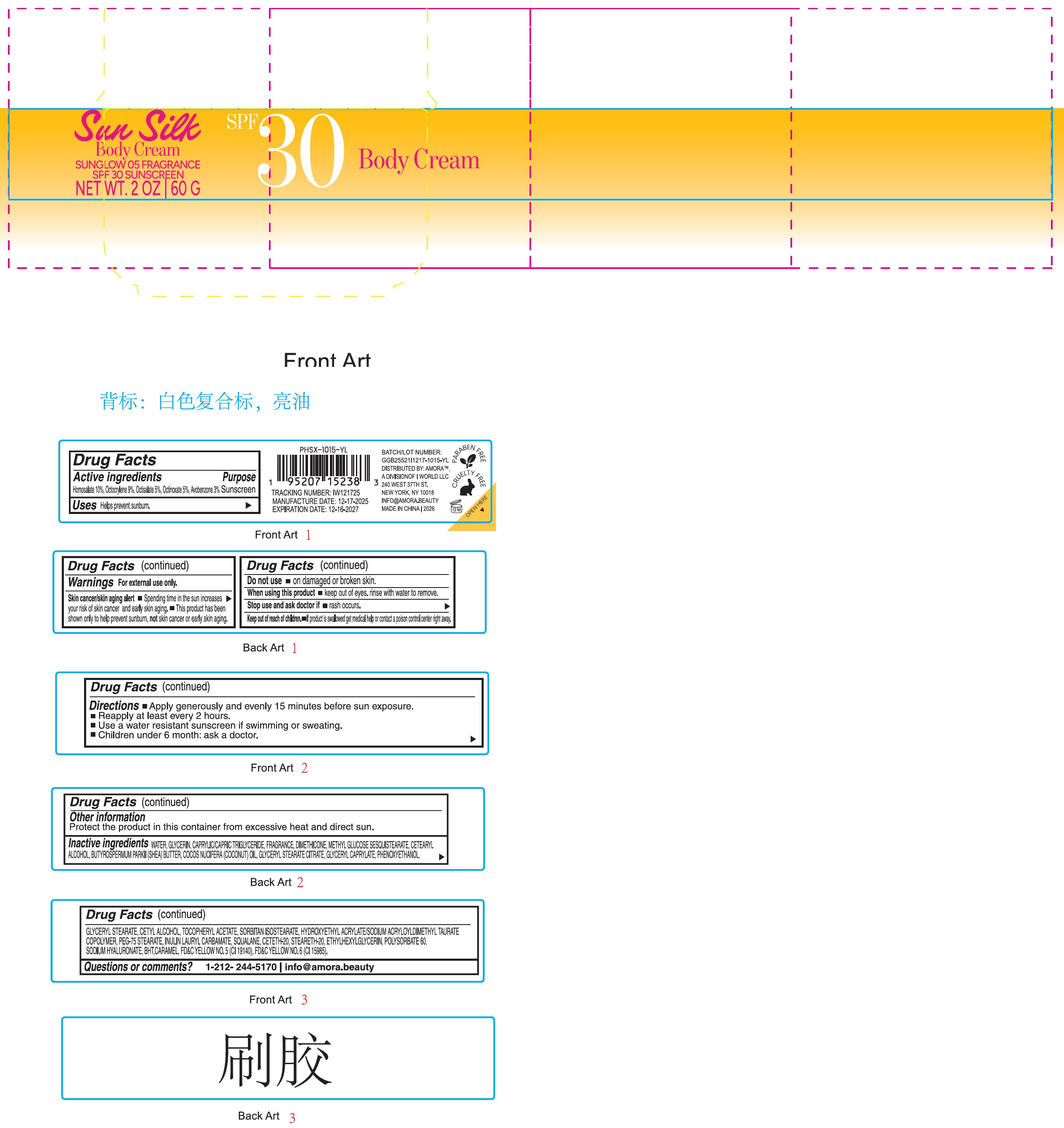 DRUG LABEL: Poolside Sun Silk Body Sunglow 05 Fragrance SPF 30 Sunscreen Body
NDC: 85179-029 | Form: LOTION
Manufacturer: I World LLC
Category: otc | Type: HUMAN OTC DRUG LABEL
Date: 20260109

ACTIVE INGREDIENTS: HOMOSALATE 100 mg/1 g; OCTOCRYLENE 90 mg/1 g; OCTISALATE 50 mg/1 g; OCTINOXATE 50 mg/1 g; AVOBENZONE 30 mg/1 g
INACTIVE INGREDIENTS: WATER; MEDIUM-CHAIN TRIGLYCERIDES; DIMETHICONE; METHYL GLUCOSE SESQUISTEARATE; CETOSTEARYL ALCOHOL; SHEA BUTTER; COCONUT OIL; GLYCERYL STEARATE CITRATE; GLYCERYL MONOCAPRYLATE; PHENOXYETHANOL; GLYCERYL MONOSTEARATE; CETYL ALCOHOL; .ALPHA.-TOCOPHEROL ACETATE; SORBITAN ISOSTEARATE; PEG-75 MONOSTEARATE; INULIN LAURYL CARBAMATE; SQUALANE; CETETH-20; STEARETH-20; ETHYLHEXYLGLYCERIN; POLYSORBATE 60; SODIUM HYALURONATE; BUTYLATED HYDROXYTOLUENE; CARAMEL; FD&C YELLOW NO. 5; FD&C YELLOW NO. 6

Poolside Sun Silk Body Cream Sunglow 05 Fragrance SPF 30 Sunscreen Body Cream

Active ingredients

Homosalate 10%, Octocrylene 9%, Octisalate 5%, Octinoxate 5%, Avobenzone 3%

Purpose

Sunscreen

Uses

Helps prevent sunburn.

Warnings

For external use only.

Skin cancer/skin aging alert

- Spending time in the sun increases your risk of skin cancer and early skin aging.
- This product has been shown only to help prevent sunburn, not skin cancer or early skin aging.

Do not use

- on damaged or broken skin.

When using this product

- keep out of eyes. rinse with water to remove.

Stop use and ask doctor if

- rash occurs.

Keep out of reach of children.

- If product is swallowed get medical help or contact a poison control center right away.

Directions

- Apply generously and evenly 15 minutes before sun exposure.
- Reapply at least every 2 hours
- Use a water resistant sunscreen if swimming or sweating.
- Children under 6 month: ask a doctor.

Other information

Protect the product in this container from excessive heat and direct sun.

Inactive ingredients

WATER, CAPRYLIC/CAPRIC TRIGLYCERIDE, FRAGRANCE, DIMETHICONE, METHYL GLUCOSIDE SESQUISTEARA, CETEARYL ALCOHOL, BUTYROSPERMUM PARKII (SHEA) BUTTER, COCOS NUCIFERA (COCONUT) OIL, GLYCERYL STEARATE CITRATE, GLYCERYL CAPRYLATE, PHENOXYETHANOL, GLYCERYL STEARATE, CETYL ALCOHOL, TOCOPHERYL ACETATE, SORBITAN ISOSTEARATE, HYDROXYETHYL ACRYLATE/SODIUM ACRYLOYLDIMETHYL TAURATE COPOLYMER, PEG-75 STEARATE, INULIN LAURYL CARBAMATE, SQUALANE, CETETH-20, STEARETH-20, ETHYLHEXYLGLYCERIN, POLYSORBATE 60, SODIUM HYALURONATE, BHT, CARAMEL, FD&C YELLOW NO. 5 (CI 19140), FD&C YELLOW NO.6 (CI 15985).

Questions or comments?

1-212- 244-5170 info@amora.beauty